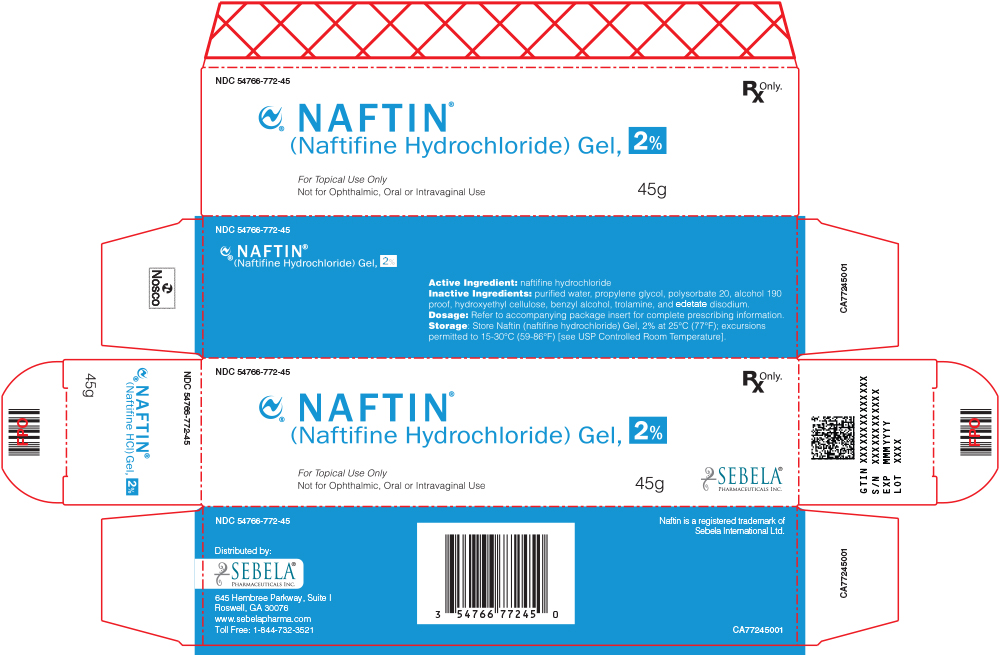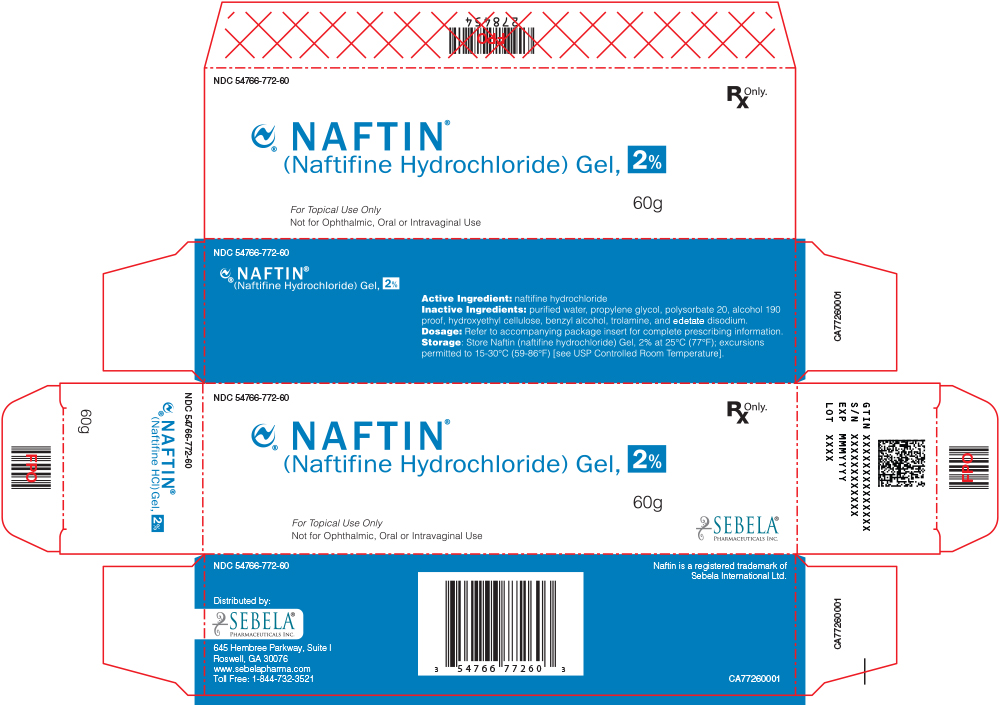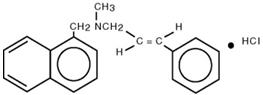 DRUG LABEL: Naftin
NDC: 54766-772 | Form: GEL
Manufacturer: Sebela Pharmaceuticals Inc.
Category: prescription | Type: HUMAN PRESCRIPTION DRUG LABEL
Date: 20251108

ACTIVE INGREDIENTS: NAFTIFINE HYDROCHLORIDE 2 g/100 g
INACTIVE INGREDIENTS: WATER; PROPYLENE GLYCOL; POLYSORBATE 20; ALCOHOL; HYDROXYETHYL CELLULOSE (2000 MPA.S AT 1%); BENZYL ALCOHOL; TROLAMINE; EDETATE DISODIUM

HIGHLIGHTS OF PRESCRIBING INFORMATION

These highlights do not include all the information needed to use NAFTIN®Gel, 2% safely and effectively. See full prescribing information for NAFTIN®(naftifine hydrochloride) Gel, 2%.
NAFTIN®(naftifine hydrochloride) gel, for topical use
Initial U.S. Approval: 1988

1 INDICATIONS AND USAGE

NAFTIN®Gel is an allylamine antifungal indicated for the treatment of interdigital tinea pedis caused by the organisms Trichophyton rubrum, Trichophyton mentagrophytes,and Epidermophyton floccosum. (1)

2 DOSAGE AND ADMINISTRATION

Apply a thin layer of NAFTIN®Gel once daily to the affected areas plus an approximate ½ inch margin of healthy surrounding skin for 2 weeks. (2)

For topical use only. NAFTIN®Gel is not for ophthalmic, oral, or intravaginal use. (2)

3 DOSAGE FORMS AND STRENGTHS

Gel, 2%. (3)

4 CONTRAINDICATIONS

None. (4)

5 WARNINGS AND PRECAUTIONS

If redness or irritation develops with the use of NAFTIN®Gel treatment should be discontinued. (5.1)

6 ADVERSE REACTIONS

The most common adverse reactions are application site reactions (2%). (6.1)

To report SUSPECTED ADVERSE REACTIONS, contact Sebela Pharmaceuticals Inc. at 1-888-271-4621 or FDA at 1-800-FDA-1088 or www.fda.gov/medwatch.

FULL PRESCRIBING INFORMATION

1 INDICATIONS AND USAGE

NAFTIN®Gel is an allylamine antifungal indicated for the treatment of interdigital tinea pedis caused by the organisms Trichophyton rubrum, Trichophyton mentagrophytes, and Epidermophyton floccosum.

2 DOSAGE AND ADMINISTRATION

Apply a thin layer of NAFTIN®Gel once daily to the affected areas plus an approximate ½ inch margin of healthy surrounding skin for 2 weeks.

For topical use only. NAFTIN®Gel is not for ophthalmic, oral, or intravaginal use.

3 DOSAGE FORMS AND STRENGTHS

Gel, 2%. Each gram contains 20 mg of naftifine hydrochloride in a colorless to yellow gel.

4 CONTRAINDICATIONS

None.

5 WARNINGS AND PRECAUTIONS

5.1 Local Adverse Reactions

If irritation or sensitivity develops with the use of NAFTIN®Gel, treatment should be discontinued.

6 ADVERSE REACTIONS

6.1 Clinical Trials Experience

Because clinical trials are conducted under widely varying conditions, adverse reaction rates observed in the clinical trials of a drug cannot be directly compared to rates in the clinical trials of another drug and may not reflect the rates observed in clinical practice.

In two randomized, vehicle-controlled trials, 1143 subjects were treated with NAFTIN®Gel versus 571 subjects treated with the vehicle. The trial subjects were 12 to 92 years old, were primarily male (76%), and were 59% Caucasian, 38% Black or African American, and 23% Hispanic or Latino. Subjects received doses once daily, topically, for 2 weeks to cover the affected skin areas plus a ½-inch margin of surrounding healthy skin. The most common adverse reactions were application site reactions which occurred at the rate of 2% in NAFTIN Gel arm versus 1% in vehicle arm. Most adverse reactions were mild in severity.

In an open-label pediatric pharmacokinetics and safety trial 22 pediatric subjects 12-17 years of age with interdigital tinea pedis received NAFTIN®Gel. The incidence of adverse reactions in the pediatric population was similar to that observed in adult population.

Cumulative irritancy testing revealed the potential for NAFTIN®Gel to cause irritation. There was no evidence that NAFTIN®Gel causes contact sensitization, phototoxicity, or photoallergenicity in healthy skin.

6.2 Postmarketing Experience

Because these reactions are reported voluntarily from a population of uncertain size, it is not always possible to reliably estimate their frequency or establish a causal relationship to drug exposure. The following adverse reactions have been identified during post-approval use of naftifine hydrochloride: blisters, burning sensation, crusting, dryness, erythema/redness, inflammation, irritation, maceration, pain, pruritus [mild]/itching, rash and swelling.

8 USE IN SPECIFIC POPULATIONS

8.1 Pregnancy

TERATOGENIC EFFECTS

Risk Summary

There are no available data on NAFTIN® Gel use in pregnant women to evaluate a drug-associated risk of major birth defects, miscarriage, or adverse maternal or fetal outcomes.

In animal reproduction studies, no adverse effects on embryofetal development were seen at oral doses administered during the period of organogenesis up to 37 times the maximum recommended human dose (MRHD) in pregnant rats or subcutaneous doses administered during the period of organogenesis up to 4 times the MRHD in pregnant rats or 7 times the MRHD in pregnant rabbits (see Data).

All pregnancies have a background risk of birth defect, loss, or other adverse outcomes. The estimated background risk of major birth defects and miscarriage for the indicated population is unknown. In the U.S. general population, the estimated background risk of major birth defects and miscarriage in clinically recognized pregnancies is 2 to 4% and 15 to 20%, respectively.

Data

Animal Data

Systemic embryofetal development studies were conducted in rats and rabbits. For the comparison of animal to human doses, the MRHD is set at 4 g 2% gel per day (1.33 mg/kg/day for a 60 kg individual).

Oral doses of 30, 100, and 300 mg/kg/day naftifine hydrochloride were administered during the period of organogenesis to pregnant female rats. No treatment-related effects on embryofetal toxicity were noted at doses up to 300 mg/kg/day (37 times the MRHD based on mg/m^2comparison). Subcutaneous doses of 10 and 30 mg/kg/day naftifine hydrochloride were administered during the period of organogenesis to pregnant female rats. No treatment-related effects on embryofetal toxicity were noted at 30 mg/kg/day (4 times the MRHD based on mg/m^2comparison). Subcutaneous doses of 3, 10, and 30 mg/kg/day naftifine hydrochloride were administered during the period of organogenesis to pregnant female rabbits. No treatment-related effects on embryofetal toxicity were noted at 30 mg/kg/day (7 times the MRHD based on mg/m^2comparison).

A peri-and post-natal development study was conducted in rats. Oral doses of 30, 100, and 300 mg/kg/day naftifine hydrochloride were administered to female rats from gestational day 14 to lactation day 21. Reduced body weight gain of females during gestation and of the offspring during lactation was noted at 300 mg/kg/day (37 times the MRHD based on mg/m^2comparison). No developmental toxicity was noted at 100 mg/kg/day (12 times the MRHD based on mg/m^2comparison).

8.2 Lactation

Risk Summary
There is no information available on the presence of naftifine hydrochloride in human milk, the effects of the drug on the breastfed infant, or the effects of the drug on milk production after topical application of NAFTIN Gel to women who are breastfeeding. It is not known whether naftifine hydrochloride is excreted in human milk. Because many drugs are excreted in human milk, caution should be exercised when naftifine hydrochloride is administered to a nursing woman.

The lack of clinical data during lactation precludes a clear determination of the risk NAFTIN Gel to an infant during lactation. Therefore, the developmental and health benefits of breastfeeding should be considered along with the mother’s clinical need for NAFTIN gel and any potential adverse effects on the breastfed infant from NAFTIN gel or from the underlying maternal condition.

8.4 Pediatric Use

The safety and effectiveness of NAFTIN® Gel have been established in the age group 12 to 18 years of age with interdigital tinea pedis.
Use of NAFTIN® Gel in this age group is supported by evidence from adequate and well controlled trials in adults with additional safety and PK data from an open label trial, conducted in 22 adolescents ≥12 years of age who were exposed to NAFTIN® Gel at a dose of approximately 4 g/day [see Clinical Pharmacology (12.3)] .

Safety and effectiveness in pediatric patients <12 years of age have not been established.

8.5 Geriatric Use

During clinical trials, 99 subjects (9%) aged 65 years and over were exposed to NAFTIN®Gel. Safety and effectiveness were similar to those reported by younger subjects.

11 DESCRIPTION

NAFTIN®Gel is a clear to yellow gel for topical use only. Each gram of NAFTIN®Gel contains 20 mg of naftifine hydrochloride, a synthetic allylamine antifungal compound.

Chemically, naftifine HCl is (E)-N-Cinnamyl-N-methyl-1-napthalenemethylamine hydrochloride.

The molecular formula is C21H21N∙HCl with a molecular weight of 323.86.

The structural formula of naftifine hydrochloride is :

NAFTIN®Gel contains the following inactive ingredients: alcohol, benzyl alcohol, edetate disodium, hydroxyethyl cellulose, purified water, propylene glycol, polysorbate 20 and trolamine.

12 CLINICAL PHARMACOLOGY

12.1 Mechanism of Action

NAFTIN®Gel is a topical antifungal drug [see Clinical Pharmacology (12.4)] .

12.2 Pharmacodynamics

The pharmacodynamics of NAFTIN®Gel have not been established .

12.3 Pharmacokinetics

In vitro and in vivo bioavailability studies have demonstrated that naftifine penetrates the stratum corneum in sufficient concentration to inhibit the growth of dermatophytes.

Pharmacokinetic analysis of plasma samples from 32 subjects with tinea pedis treated with a mean dose of 3.9 grams NAFTIN®Gel applied once daily to both feet for 14 days showed increased exposure over the treatment period, with a geometric mean (CV%) AUC0-24(area under plasma concentration-versus-time curve from time 0 to 24 hours) of 10.5 (118) ng∙hr/mL on Day 1 and an AUC0-24of 70 (59) ng∙hr/mL on Day 14. The accumulation ratio based on AUC was approximately 6.

Maximum concentration (Cmax) also increased over the treatment period; geometric mean (CV%) Cmaxafter a single dose was 0.9 (92) ng/mL on Day 1; Cmaxon Day 14 was 3.7 (64) ng/mL. Median Tmaxwas 20.0 hours (range: 8, 20 hours) after a single application on Day 1 and 8.0 hours (range: 0, 24 hours) on Day 14. Trough plasma concentrations increased during the trial period and reached steady state after 11 days. In the same pharmacokinetic trial the fraction of dose excreted in urine during the treatment period was less than or equal to 0.01% of the applied dose.

In a second trial, the pharmacokinetics of NAFTIN®Gel was evaluated in 22 pediatric subjects 12-17 years of age with tinea pedis. Subjects were treated with a mean dose of 4.1 grams NAFTIN®Gel applied to the affected area once daily for 14 days. The results showed that the systemic exposure increased over the treatment period. Geometric mean (CV%) AUC0-24 was 15.9 (212) ng∙hr/mL on Day 1 and 60.0 (131) ng∙hr/mL on Day 14. Geometric mean (CV%) Cmax after a single dose was 1.40 (154) ng/mL on Day 1 and 3.81 (154) ng/mL on Day 14. The fraction of dose excreted in urine during the treatment period was less than or equal to 0.003% of the applied dose.

12.4 Microbiology

Mechanism of Action

Naftifine is an antifungal that belongs to the allylamine class. Although the exact mechanism of action against fungi is not known, naftifine hydrochloride appears to interfere with sterol biosynthesis by inhibiting the enzyme squalene 2, 3-epoxidase. The inhibition of enzyme activity by this allylamine results in decreased amounts of sterols, especially ergosterol, and a corresponding accumulation of squalene in the cells.

Mechanism of Resistance

To date, a mechanism of resistance to naftifine has not been identified.

Naftifine has been shown to be active against most isolates of the following fungi, both in vitro and in clinical infections, as described in the INDICATIONS AND USAGE section:

- Trichophyton rubrum
- Trichophyton mentagrophytes
- Epidermophyton floccosum

13 NONCLINICAL TOXICOLOGY

13.1 Carcinogenesis, Mutagenesis, Impairment of Fertility

In a 2-year dermal carcinogenicity study, naftifine hydrochloride cream was administered to Sprague-Dawley rats at topical doses of 1%, 2% and 3% (10, 20, and 30 mg/kg/day naftifine hydrochloride). No drug-related tumors were noted in this study up to the highest dose evaluated in this study of 30 mg/kg/day (36 times the MRHD based on AUC comparison).

Naftifine hydrochloride revealed no evidence of mutagenic or clastogenic potential based on the results of two in vitro genotoxicity tests (Ames assay and Chinese hamster ovary cell chromosome aberration assay) and one in vivo genotoxicity test (mouse bone marrow micronucleus assay).

Oral administration of naftifine hydrochloride to rats, throughout mating, gestation, parturition, and lactation, demonstrated no effects on growth, fertility, or reproduction, at doses up to 100 mg/kg/day (12 times the MRHD based on mg/m^2 comparison).

14 CLINICAL STUDIES

NAFTIN® Gel has been evaluated for efficacy in two randomized, double-blind, vehicle-controlled, multicenter trials that included 1175 subjects with symptomatic and dermatophyte culture-positive interdigital tinea pedis. Subjects were randomized to receive NAFTIN®Gel or vehicle. Subjects applied naftifine hydrochloride gel 2% or vehicle to the affected area of the foot once daily for 2 weeks. Signs and symptoms of interdigital tinea pedis (presence or absence of erythema, pruritus, and scaling) were assessed and potassium hydroxide (KOH) examination and dermatophyte culture were performed 6 weeks after the first treatment.

The mean age of the study population was 45 years; 77% were male; and 60% were Caucasian, 35% were Black or African American, and 26% were Hispanic or Latino. At baseline, subjects were confirmed to have signs and symptoms of interdigital tinea pedis, positive KOH exam, and confirmed dermatophyte culture. The primary efficacy endpoint was the proportion of subjects with a complete cure at 6 weeks after the start of treatment (4 weeks after the last treatment). Complete cure was defined as both a clinical cure (absence of erythema, pruritus, and scaling) and mycological cure (negative KOH and dermatophyte culture).

The efficacy results at week 6, four weeks following the end of treatment, are presented in Table 1 below.

Table 1 Interdigital Tinea Pedis: Number (%) of Subjects with Complete Cure, Effective Treatment, and Mycological Cure at Week 6 Following Treatment with NAFTIN®Gel (Full Analysis Set, Missing Values Treated as Treatment Failure)
 | Trial 1 |  | Trial 2
Endpoint | NAFTIN®Gel, 2% N=382 n (%) | Vehicle N=179 n (%) | NAFTIN®Gel, 2% N=400 n (%) | Vehicle N=213 n (%)
Complete Cure [Complete cure is a composite endpoint of both mycological cure and clinical cure. Clinical cure is defined as the absence of erythema, pruritus, and scaling (grade of 0).] | 64 (17%) | 3 (2%) | 104 (26%) | 7 (3%)
Treatment Effectiveness [Effective treatment is a negative KOH preparation and negative dermatophyte culture, erythema, scaling, and pruritus grades of 0 or 1 (absent or nearly absent).] | 207 (54%) | 11 (6%) | 203 (51%) | 15 (7%)
Mycological Cure [Mycological cure is defined as negative KOH and dermatophyte culture.] | 250 (65%) | 25 (14%) | 235 (59%) | 22 (10%)

16 HOW SUPPLIED/STORAGE AND HANDLING

How Supplied

NAFTIN®Gel is a colorless to yellow gel supplied in collapsible tubes in the following size:
45g – NDC 54766-772-45
60g – NDC 54766-772-60

Storage

Store NAFTIN®Gel at 25°C (77°F); excursions permitted to 15-30°C (59-86°F) [see USP Controlled Room Temperature].

17 PATIENT COUNSELING INFORMATION

- Inform patients that NAFTIN®Gel is for topical use only. NAFTIN®Gel is not intended for ophthalmic, oral, or intravaginal use.
- Patients should be directed to contact their physician if irritation develops with the use of NAFTIN®Gel.

Distributed by Sebela Pharmaceuticals Inc.

645 Hembree Parkway, Suite I, Roswell, GA 30076

www.sebelapharma.com

Toll Free 1-844-732-3521
©2020 Sebela Pharmaceuticals Inc. All rights reserved.

PRINCIPAL DISPLAY PANEL - 45g Tube Carton

NDC 54766-772-45

NAFTIN ®
(Naftifine Hydrochloride) Gel, 2%

Sebela Pharmaceuticals Inc.

For Topical Use Only
Not for Ophthalmic, Oral or Intravaginal Use

45g
Rx Only

PRINCIPAL DISPLAY PANEL - 60 g Tube Carton

NDC 54766-772-60

NAFTIN®
(Naftifine Hydrochloride) Gel, 2%

Sebela Pharmaceuticals Inc.

For Topical Use Only
Not for Ophthalmic, Oral or Intravaginal Use

60g
Rx Only